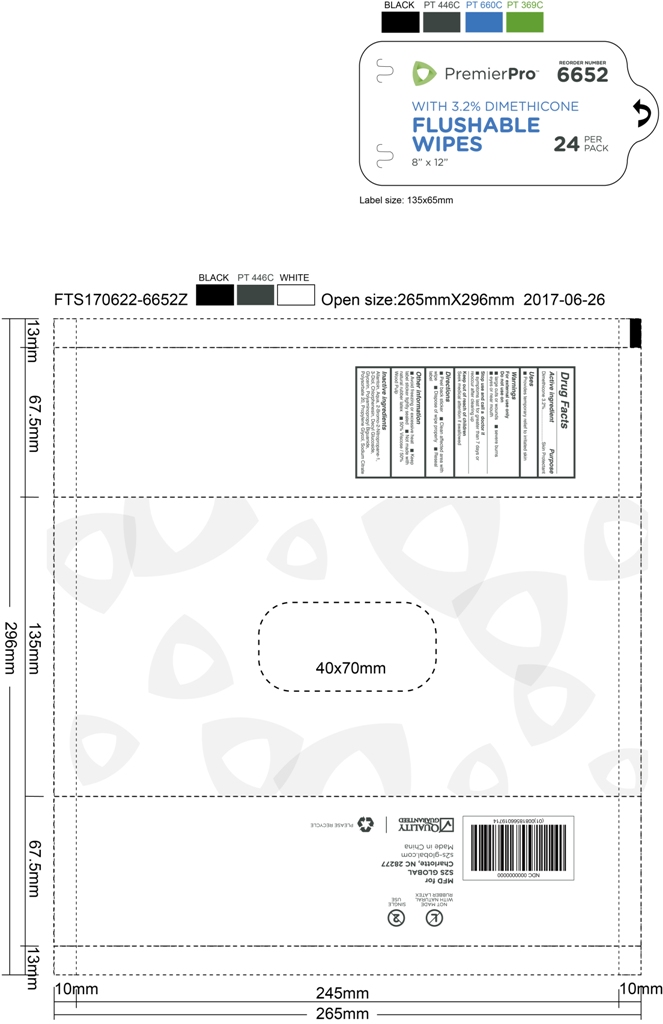 DRUG LABEL: Flushable wipes
NDC: 69392-901 | Form: GEL
Manufacturer: SVS, LLC (DBA S2S Global)
Category: otc | Type: HUMAN OTC DRUG LABEL
Date: 20180106

ACTIVE INGREDIENTS: DIMETHICONE 3.2 g/100 g
INACTIVE INGREDIENTS: SODIUM CITRATE; POLIHEXANIDE HYDROCHLORIDE; PROPYLENE GLYCOL; DECYL GLUCOSIDE; ALLANTOIN; WATER; GLYCERIN; CHLORPHENESIN; BRONOPOL; POLYSORBATE 20

Active Ingredient

Dimethicone 3.2%

Purpose

Skin Protectant

Use

provides temporary relief to irritated skin

Warning

For external use only
Do not use on

Large cuts or wounds

severe burns

eyes or near mouth

stop use and call a doctor if

symptoms last for greater than 7 days or reoccur after clearing up

Keep out of reach of children ,seek medical attention if swallowed

Directions

peel back sticker

clean affected area with wipe

dispose of wipe properly

reseal label

INACTIVE INGREDIENT

Aqua
Glycerin
Propylene Glycol
Polyaminopropyl Biguanide
Polysorbate 20
Allantoin
Chlorphenesin
Decyl Glucoside
2-Bromo-2-Nitropropane-1,3-Diol
Sodium Citrate